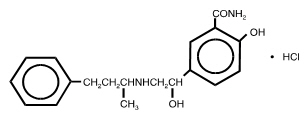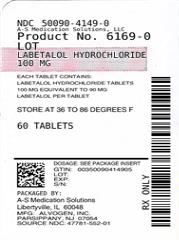 DRUG LABEL: Labetalol Hydrochloride
NDC: 50090-4149 | Form: TABLET, FILM COATED
Manufacturer: A-S Medication Solutions
Category: prescription | Type: HUMAN PRESCRIPTION DRUG LABEL
Date: 20210301

ACTIVE INGREDIENTS: LABETALOL HYDROCHLORIDE 100 mg/1 1
INACTIVE INGREDIENTS: STARCH, CORN; HYPROMELLOSE 2910 (6 MPA.S); LACTOSE, UNSPECIFIED FORM; MAGNESIUM STEARATE; FD&C YELLOW NO. 6; TALC; TITANIUM DIOXIDE

Labetalol Hydrochloride Tablets

DESCRIPTION

Labetalol Hydrochloride Tablets are adrenergic receptor blocking agents that have both selective alpha1-adrenergic and nonselective beta-adrenergic receptor blocking actions in a single substance.

Labetalol hydrochloride (HCl) is a racemate chemically designated as 2-hydroxy-5-[1-hydroxy-2-[(1-methyl-3-phenylpropyl)amino]ethyl]benzamide monohydrochloride, and it has the following structure:

Labetalol HCl has the empirical formula C19H24N2O3∙HCl and a molecular weight of 364.9. It has two asymmetric centers and therefore exists as a molecular complex of two diastereoisomeric pairs. Dilevalol, the R,R´ stereoisomer, makes up 25% of racemic labetalol.

Labetalol HCl is a white or off-white crystalline powder, soluble in water.

Labetalol Hydrochloride Tablets contain 100 mg, 200 mg, or 300 mg of labetalol HCl and are taken orally. The tablets also contain the inactive ingredients corn starch, FD&C Yellow No. 6 (100-mg and 300-mg tablets only), hydroxypropyl methylcellulose, lactose, magnesium stearate, pregelatinized corn starch, sodium benzoate (200-mg tablet only), talc (100-mg tablet only), and titanium dioxide.

CLINICAL PHARMACOLOGY

Labetalol HCl combines both selective, competitive, alpha1-adrenergic blocking and nonselective, competitive, beta-adrenergic blocking activity in a single substance. In man, the ratios of alpha- to beta-blockade have been estimated to be approximately 1:3 and 1:7 following oral and intravenous (IV) administration, respectively. Beta2-agonist activity has been demonstrated in animals with minimal beta1-agonist (ISA) activity detected. In animals, at doses greater than those required for alpha- or beta-adrenergic blockade, a membrane stabilizing effect has been demonstrated.

Pharmacodynamics

The capacity of labetalol HCl to block alpha receptors in man has been demonstrated by attenuation of the pressor effect of phenylephrine and by a significant reduction of the pressor response caused by immersing the hand in ice-cold water ("cold-pressor test"). Labetalol HCl's beta1-receptor blockade in man was demonstrated by a small decrease in the resting heart rate, attenuation of tachycardia produced by isoproterenol or exercise, and by attenuation of the reflex tachycardia to the hypotension produced by amyl nitrite. Beta2-receptor blockade was demonstrated by inhibition of the isoproterenol-induced fall in diastolic blood pressure. Both the alpha- and beta-blocking actions of orally administered labetalol HCl contribute to a decrease in blood pressure in hypertensive patients. Labetalol HCl consistently, in dose-related fashion, blunted increases in exercise-induced blood pressure and heart rate, and in their double product. The pulmonary circulation during exercise was not affected by labetalol HCl dosing.

Single oral doses of labetalol HCl administered to patients with coronary artery disease had no significant effect on sinus rate, intraventricular conduction, or QRS duration. The atrioventricular (A-V) conduction time was modestly prolonged in two of seven patients. In another study, IV labetalol HCl slightly prolonged A-V nodal conduction time and atrial effective refractory period with only small changes in heart rate. The effects on A-V nodal refractoriness were inconsistent.

Labetalol HCl produces dose-related falls in blood pressure without reflex tachycardia and without significant reduction in heart rate, presumably through a mixture of its alpha- and beta-blocking effects. Hemodynamic effects are variable, with small, nonsignificant changes in cardiac output seen in some studies but not others, and small decreases in total peripheral resistance. Elevated plasma renins are reduced.

Doses of labetalol HCl that controlled hypertension did not affect renal function in mildly to severely hypertensive patients with normal renal function.

Due to the alpha1-receptor blocking activity of labetalol HCl, blood pressure is lowered more in the standing than in the supine position, and symptoms of postural hypotension (2%), including rare instances of syncope, can occur. Following oral administration, when postural hypotension has occurred, it has been transient and is uncommon when the recommended starting dose and titration increments are closely followed (see DOSAGE AND ADMINISTRATION). Symptomatic postural hypotension is most likely to occur 2 to 4 hours after a dose, especially following the use of large initial doses or upon large changes in dose.

The peak effects of single oral doses of labetalol HCl occur within 2 to 4 hours. The duration of effect depends upon dose, lasting at least 8 hours following single oral doses of 100 mg and more than 12 hours following single oral doses of 300 mg. The maximum, steady-state blood pressure response upon oral, twice-a-day dosing occurs within 24 to 72 hours.

The antihypertensive effect of labetalol has a linear correlation with the logarithm of labetalol plasma concentration, and there is also a linear correlation between the reduction in exercise-induced tachycardia occurring at 2 hours after oral administration of labetalol HCl and the logarithm of the plasma concentration.

About 70% of the maximum beta-blocking effect is present for 5 hours after the administration of a single oral dose of 400 mg with suggestion that about 40% remains at 8 hours.

The antianginal efficacy of labetalol HCl has not been studied. In 37 patients with hypertension and coronary artery disease, labetalol HCl did not increase the incidence or severity of angina attacks.

Exacerbation of angina and, in some cases, myocardial infarction and ventricular dysrhythmias have been reported after abrupt discontinuation of therapy with beta-adrenergic blocking agents in patients with coronary artery disease. Abrupt withdrawal of these agents in patients without coronary artery disease has resulted in transient symptoms, including tremulousness, sweating, palpitation, headache, and malaise. Several mechanisms have been proposed to explain these phenomena, among them increased sensitivity to catecholamines because of increased numbers of beta receptors.

Although beta-adrenergic receptor blockade is useful in the treatment of angina and hypertension, there are also situations in which sympathetic stimulation is vital. For example, in patients with severely damaged hearts, adequate ventricular function may depend on sympathetic drive. Beta-adrenergic blockade may worsen A-V block by preventing the necessary facilitating effects of sympathetic activity on conduction. Beta2-adrenergic blockade results in passive bronchial constriction by interfering with endogenous adrenergic bronchodilator activity in patients subject to bronchospasm, and it may also interfere with exogenous bronchodilators in such patients.

Pharmacokinetics and Metabolism

Labetalol HCl is completely absorbed from the gastrointestinal tract with peak plasma levels occurring 1 to 2 hours after oral administration. The relative bioavailability of labetalol HCl tablets compared to an oral solution is 100%. The absolute bioavailability (fraction of drug reaching systemic circulation) of labetalol when compared to an IV infusion is 25%; this is due to extensive "first-pass" metabolism. Despite "first-pass" metabolism, there is a linear relationship between oral doses of 100 mg to 3,000 mg and peak plasma levels. The absolute bioavailability of labetalol is increased when administered with food.

The plasma half-life of labetalol following oral administration is about 6 to 8 hours. Steady-state plasma levels of labetalol during repetitive dosing are reached by about the third day of dosing. In patients with decreased hepatic or renal function, the elimination half-life of labetalol is not altered; however, the relative bioavailability in hepatically impaired patients is increased due to decreased "first-pass" metabolism.

The metabolism of labetalol is mainly through conjugation to glucuronide metabolites. These metabolites are present in plasma and are excreted in the urine and, via the bile, into the feces. Approximately 55% to 60% of a dose appears in the urine as conjugates or unchanged labetalol within the first 24 hours of dosing.

Labetalol has been shown to cross the placental barrier in humans. Only negligible amounts of the drug crossed the blood-brain barrier in animal studies. Labetalol is approximately 50% protein bound. Neither hemodialysis nor peritoneal dialysis removes a significant amount of labetalol HCl from the general circulation (<1%).

Elderly Patients

Some pharmacokinetic studies indicate that the elimination of labetalol is reduced in elderly patients. Therefore, although elderly patients may initiate therapy at the currently recommended dosage of 100 mg twice daily, elderly patients will generally require lower maintenance dosages than nonelderly patients.

INDICATIONS AND USAGE

Labetalol Hydrochloride Tablets are indicated in the management of hypertension. Labetalol Hydrochloride Tablets may be used alone or in combination with other antihypertensive agents, especially thiazide and loop diuretics.

CONTRAINDICATIONS

Labetalol Hydrochloride Tablets are contraindicated in bronchial asthma, overt cardiac failure, greater-than-first-degree heart block, cardiogenic shock, severe bradycardia, other conditions associated with severe and prolonged hypotension, and in patients with a history of hypersensitivity to any component of the product (see WARNINGS).

Beta-blockers, even those with apparent cardioselectivity, should not be used in patients with a history of obstructive airway disease, including asthma.

WARNINGS

Hepatic Injury

Severe hepatocellular injury, confirmed by rechallenge in at least one case, occurs rarely with labetalol therapy. The hepatic injury is usually reversible, but hepatic necrosis and death have been reported. Injury has occurred after both short- and long-term treatment and may be slowly progressive despite minimal symptomatology. Similar hepatic events have been reported with a related research compound, dilevalol HCl, including two deaths. Dilevalol HCl is one of the four isomers of labetalol HCl. Thus, for patients taking labetalol, periodic determination of suitable hepatic laboratory tests would be appropriate. Appropriate laboratory testing should be done at the first symptom/sign of liver dysfunction (e.g., pruritus, dark urine, persistent anorexia, jaundice, right upper quadrant tenderness, or unexplained "flu-like" symptoms). If the patient has laboratory evidence of liver injury or jaundice, labetalol should be stopped and not restarted.

Cardiac Failure

Sympathetic stimulation is a vital component supporting circulatory function in congestive heart failure. Beta-blockade carries a potential hazard of further depressing myocardial contractility and precipitating more severe failure. Although beta-blockers should be avoided in overt congestive heart failure, if necessary, labetalol HCl can be used with caution in patients with a history of heart failure who are well compensated. Congestive heart failure has been observed in patients receiving labetalol HCl. Labetalol HCl does not abolish the inotropic action of digitalis on heart muscle.

In Patients Without a History of Cardiac Failure

In patients with latent cardiac insufficiency, continued depression of the myocardium with beta-blocking agents over a period of time can, in some cases, lead to cardiac failure. At the first sign or symptom of impending cardiac failure, patients should be fully digitalized and/or be given a diuretic, and the response should be observed closely. If cardiac failure continues despite adequate digitalization and diuretic, therapy with Labetalol Hydrochloride Tablets should be withdrawn (gradually, if possible).

Exacerbation of Ischemic Heart Disease Following Abrupt Withdrawal

Angina pectoris has not been reported upon labetalol HCl discontinuation. However, hypersensitivity to catecholamines has been observed in patients withdrawn from beta-blocker therapy; exacerbation of angina and, in some cases, myocardial infarction have occurred after abrupt discontinuation of such therapy. When discontinuing chronically administered Labetalol Hydrochloride Tablets, particularly in patients with ischemic heart disease, the dosage should be gradually reduced over a period of 1 to 2 weeks and the patient should be carefully monitored. If angina markedly worsens or acute coronary insufficiency develops, therapy with Labetalol Hydrochloride Tablets should be reinstituted promptly, at least temporarily, and other measures appropriate for the management of unstable angina should be taken. Patients should be warned against interruption or discontinuation of therapy without the physician's advice. Because coronary artery disease is common and may be unrecognized, it may be prudent not to discontinue therapy with Labetalol Hydrochloride Tablets abruptly in patients being treated for hypertension.

Nonallergic Bronchospasm (e.g., Chronic Bronchitis and Emphysema)

Patients with bronchospastic disease should, in general, not receive beta-blockers. Labetalol Hydrochloride Tablets may be used with caution, however, in patients who do not respond to, or cannot tolerate, other antihypertensive agents. It is prudent, if Labetalol Hydrochloride Tablets are used, to use the smallest effective dose, so that inhibition of endogenous or exogenous beta-agonists is minimized.

Pheochromocytoma

Labetalol HCl has been shown to be effective in lowering blood pressure and relieving symptoms in patients with pheochromocytoma. However, paradoxical hypertensive responses have been reported in a few patients with this tumor; therefore, use caution when administering labetalol HCl to patients with pheochromocytoma.

Diabetes Mellitus and Hypoglycemia

Beta-adrenergic blockade may prevent the appearance of premonitory signs and symptoms (e.g., tachycardia) of acute hypoglycemia. This is especially important with labile diabetics. Beta-blockade also reduces the release of insulin in response to hyperglycemia; it may therefore be necessary to adjust the dose of antidiabetic drugs.

Major Surgery

Do not routinely withdraw chronic beta blocker therapy prior to surgery. The effect of labetalol's alpha adrenergic activity has not been evaluated in this setting.

A synergism between labetalol HCl and halothane anesthesia has been shown (see PRECAUTIONS: Drug Interactions).

PRECAUTIONS

General

Impaired Hepatic Function: Labetalol Hydrochloride Tablets should be used with caution in patients with impaired hepatic function since metabolism of the drug may be diminished.

Intraoperative Floppy Iris Syndrome (IFIS) has been observed during cataract surgery in some patients treated with alpha-1 blockers (labetalol is an alpha/beta blocker). This variant of small pupil syndrome is characterized by the combination of a flaccid iris that billows in response to intraoperative irrigation currents, progressive intraoperative miosis despite preoperative dilation with standard mydriatic drugs, and potential prolapse of the iris toward the phacoemulsification incisions. The patient's ophthalmologist should be prepared for possible modifications to the surgical technique, such as the utilization of iris hooks, iris dilator rings, or viscoelastic substances. There does not appear to be a benefit of stopping alpha-1 blocker therapy prior to cataract surgery.

Jaundice or Hepatic Dysfunction: (see WARNINGS).

Information for Patients

As with all drugs with beta-blocking activity, certain advice to patients being treated with labetalol HCl is warranted. This information is intended to aid in the safe and effective use of this medication. It is not a disclosure of all possible adverse or intended effects. While no incident of the abrupt withdrawal phenomenon (exacerbation of angina pectoris) has been reported with labetalol HCl, dosing with Labetalol Hydrochloride Tablets should not be interrupted or discontinued without a physician's advice. Patients being treated with Labetalol Hydrochloride Tablets should consult a physician at any signs or symptoms of impending cardiac failure or hepatic dysfunction (see WARNINGS). Also, transient scalp tingling may occur, usually when treatment with Labetalol Hydrochloride Tablets is initiated (see ADVERSE REACTIONS).

Laboratory Tests

As with any new drug given over prolonged periods, laboratory parameters should be observed over regular intervals. In patients with concomitant illnesses, such as impaired renal function, appropriate tests should be done to monitor these conditions.

Drug Interactions

In one survey, 2.3% of patients taking labetalol HCl in combination with tricyclic antidepressants experienced tremor, as compared to 0.7% reported to occur with labetalol HCl alone. The contribution of each of the treatments to this adverse reaction is unknown, but the possibility of a drug interaction cannot be excluded.

Drugs possessing beta-blocking properties can blunt the bronchodilator effect of beta-receptor agonist drugs in patients with bronchospasm; therefore, doses greater than the normal antiasthmatic dose of beta-agonist bronchodilator drugs may be required.

Cimetidine has been shown to increase the bioavailability of labetalol HCl. Since this could be explained either by enhanced absorption or by an alteration of hepatic metabolism of labetalol HCl, special care should be used in establishing the dose required for blood pressure control in such patients.

Synergism has been shown between halothane anesthesia and intravenously administered labetalol HCl. During controlled hypotensive anesthesia using labetalol HCl in association with halothane, high concentrations (3% or above) of halothane should not be used because the degree of hypotension will be increased and because of the possibility of a large reduction in cardiac output and an increase in central venous pressure. The anesthesiologist should be informed when a patient is receiving labetalol HCl.

Labetalol HCl blunts the reflex tachycardia produced by nitroglycerin without preventing its hypotensive effect. If labetalol HCl is used with nitroglycerin in patients with angina pectoris, additional antihypertensive effects may occur.

Care should be taken if labetalol is used concomitantly with calcium antagonists of the verapamil type.

Both digitalis glycosides and beta-blockers slow atrioventricular conduction and decrease heart rate. Concomitant use can increase the risk of bradycardia.

Risk of Anaphylactic Reaction

While taking beta-blockers, patients with a history of severe anaphylactic reaction to a variety of allergens may be more reactive to repeated challenge, either accidental, diagnostic, or therapeutic. Such patients may be unresponsive to the usual doses of epinephrine used to treat allergic reaction.

Drug/Laboratory Test Interactions

The presence of labetalol metabolites in the urine may result in falsely elevated levels of urinary catecholamines, metanephrine, normetanephrine, and vanillylmandelic acid when measured by fluorimetric or photometric methods. In screening patients suspected of having a pheochromocytoma and being treated with labetalol HCl, a specific method, such as a high performance liquid chromatographic assay with solid phase extraction (e.g., J Chromatogr 385:241,1987) should be employed in determining levels of catecholamines.

Labetalol HCl has also been reported to produce a false-positive test for amphetamine when screening urine for the presence of drugs using the commercially available assay methods TOXI-LAB® A (thin-layer chromatographic assay) and EMIT-d.a.u.® (radioenzymatic assay). When patients being treated with labetalol have a positive urine test for amphetamine using these techniques, confirmation should be made by using more specific methods, such as a gas chromatographic-mass spectrometer technique.

Carcinogenesis, Mutagenesis, Impairment of Fertility

Long-term oral dosing studies with labetalol HCl for 18 months in mice and for 2 years in rats showed no evidence of carcinogenesis. Studies with labetalol HCl using dominant lethal assays in rats and mice and exposing microorganisms according to modified Ames tests showed no evidence of mutagenesis.

Pregnancy

Teratogenic Effects

Pregnancy Category C

Teratogenic studies were performed with labetalol in rats and rabbits at oral doses up to approximately six and four times the maximum recommended human dose (MRHD), respectively. No reproducible evidence of fetal malformations was observed. Increased fetal resorptions were seen in both species at doses approximating the MRHD. A teratology study performed with labetalol in rabbits at IV doses up to 1.7 times the MRHD revealed no evidence of drug-related harm to the fetus. There are no adequate and well-controlled studies in pregnant women. Labetalol should be used during pregnancy only if the potential benefit justifies the potential risk to the fetus.

Nonteratogenic Effects

Hypotension, bradycardia, hypoglycemia, and respiratory depression have been reported in infants of mothers who were treated with labetalol HCl for hypertension during pregnancy. Oral administration of labetalol to rats during late gestation through weaning at doses of two to four times the MRHD caused a decrease in neonatal survival.

Labor and Delivery

Labetalol HCl given to pregnant women with hypertension did not appear to affect the usual course of labor and delivery.

Nursing Mothers

Small amounts of labetalol (approximately 0.004% of the maternal dose) are excreted in human milk. Caution should be exercised when Labetalol Hydrochloride Tablets are administered to a nursing woman.

Pediatric Use

Safety and effectiveness in pediatric patients have not been established.

Elderly Patients

As in the general population, some elderly patients (60 years of age and older) have experienced orthostatic hypotension, dizziness, or lightheadedness during treatment with labetalol. Because elderly patients are generally more likely than younger patients to experience orthostatic symptoms, they should be cautioned about the possibility of such side effects during treatment with labetalol.

ADVERSE REACTIONS

Most adverse effects are mild and transient and occur early in the course of treatment. In controlled clinical trials of 3 to 4 months' duration, discontinuation of Labetalol Hydrochloride Tablets due to one or more adverse effects was required in 7% of all patients. In these same trials, other agents with solely beta‑blocking activity used in the control groups led to discontinuation in 8% to 10% of patients, and a centrally acting alpha‑agonist led to discontinuation in 30% of patients.

The incidence rates of adverse reactions listed in the following table were derived from multicenter, controlled clinical trials comparing labetalol HCl, placebo, metoprolol, and propranolol over treatment periods of 3 and 4 months. Where the frequency of adverse effects for labetalol HCl and placebo is similar, causal relationship is uncertain. The rates are based on adverse reactions considered probably drug related by the investigator. If all reports are considered, the rates are somewhat higher (e.g., dizziness, 20%; nausea, 14%; fatigue, 11%), but the overall conclusions are unchanged.

 | Labetalol HCl (n = 227) % | Placebo (n = 98) % | Propranolol (n = 84) % | Metoprolol (n = 49) %
Body as a whole
Fatigue | 5 | 0 | 12 | 12
Asthenia | 1 | 1 | 1 | 0
Headache | 2 | 1 | 1 | 2
Gastrointestinal
Nausea | 6 | 1 | 1 | 2
Vomiting | <1 | 0 | 0 | 0
Dyspepsia | 3 | 1 | 1 | 0
Abdominal pain | 0 | 0 | 1 | 2
Diarrhea | <1 | 0 | 2 | 0
Taste distortion | 1 | 0 | 0 | 0
Central and peripheral nervous systems
Dizziness | 11 | 3 | 4 | 4
Paresthesia | <1 | 0 | 0 | 0
Drowsiness | <1 | 2 | 2 | 2
Autonomic nervous system
Nasal stuffiness | 3 | 0 | 0 | 0
Ejaculation failure | 2 | 0 | 0 | 0
Impotence | 1 | 0 | 1 | 3
Increased sweating | <1 | 0 | 0 | 0
Cardiovascular
Edema | 1 | 0 | 0 | 0
Postural hypotension | 1 | 0 | 0 | 0
Bradycardia | 0 | 0 | 5 | 12
Respiratory
Dyspnea | 2 | 0 | 1 | 2
Skin
Rash | 1 | 0 | 0 | 0
Special senses
Vision abnormality | 1 | 0 | 0 | 0
Vertigo | 2 | 1 | 0 | 0

The adverse effects were reported spontaneously and are representative of the incidence of adverse effects that may be observed in a properly selected hypertensive patient population, i.e., a group excluding patients with bronchospastic disease, overt congestive heart failure, or other contraindications to beta-blocker therapy.

Clinical trials also included studies utilizing daily doses up to 2,400 mg in more severely hypertensive patients. Certain of the side effects increased with increasing dose, as shown in the following table that depicts the entire US therapeutic trials data base for adverse reactions that are clearly or possibly dose related.

Labetalol HCl Daily Dose (mg) | 200 | 300 | 400 | 600 | 800 | 900 | 1,200 | 1,600 | 2,400
Number of patients | 522 | 181 | 606 | 608 | 503 | 117 | 411 | 242 | 175
Dizziness (%) | 2 | 3 | 3 | 3 | 5 | 1 | 9 | 13 | 16
Fatigue | 2 | 1 | 4 | 4 | 5 | 3 | 7 | 6 | 10
Nausea | <1 | 0 | 1 | 2 | 4 | 0 | 7 | 11 | 19
Vomiting | 0 | 0 | <1 | <1 | <1 | 0 | 1 | 2 | 3
Dyspepsia | 1 | 0 | 2 | 1 | 1 | 0 | 2 | 2 | 4
Paresthesia | 2 | 0 | 2 | 2 | 1 | 1 | 2 | 5 | 5
Nasal stuffiness | 1 | 1 | 2 | 2 | 2 | 2 | 4 | 5 | 6
Ejaculation failure | 0 | 2 | 1 | 2 | 3 | 0 | 4 | 3 | 5
Impotence | 1 | 1 | 1 | 1 | 2 | 4 | 3 | 4 | 3
Edema | 1 | 0 | 1 | 1 | 1 | 0 | 1 | 2 | 2

In addition, a number of other less common adverse events have been reported:

Body as a Whole: Fever.

Cardiovascular: Hypotension, and rarely, syncope, bradycardia, heart block.

Central and Peripheral Nervous Systems: Paresthesia, most frequently described as scalp tingling. In most cases, it was mild and transient and usually occurred at the beginning of treatment.

Collagen Disorders: Systemic lupus erythematosus, positive antinuclear factor.

Eyes: Dry eyes.

Immunological System: Antimitochondrial antibodies.

Liver and Biliary System: Hepatic necrosis, hepatitis, cholestatic jaundice, elevated liver function tests.

Musculoskeletal System: Muscle cramps, toxic myopathy.

Respiratory System: Bronchospasm.

Skin and Appendages: Rashes of various types, such as generalized maculopapular, lichenoid, urticarial, bullous lichen planus, psoriaform, and facial erythema; Peyronie's disease; reversible alopecia.

Urinary System: Difficulty in micturition, including acute urinary bladder retention.

Hypersensitivity: Rare reports of hypersensitivity (e.g., rash, urticaria, pruritus, angioedema, dyspnea) and anaphylactoid reactions.

Following approval for marketing in the United Kingdom, a monitored release survey involving approximately 6,800 patients was conducted for further safety and efficacy evaluation of this product. Results of this survey indicate that the type, severity, and incidence of adverse effects were comparable to those cited above.

Potential Adverse Effects: In addition, other adverse effects not listed above have been reported with other beta-adrenergic blocking agents.

Central Nervous System: Reversible mental depression progressing to catatonia, an acute reversible syndrome characterized by disorientation for time and place, short-term memory loss, emotional lability, slightly clouded sensorium, and decreased performance on psychometrics.

Cardiovascular: Intensification of A-V block (see CONTRAINDICATIONS).

Allergic: Fever combined with aching and sore throat, laryngospasm, respiratory distress.

Hematologic: Agranulocytosis, thrombocytopenic or nonthrombocytopenic purpura.

Gastrointestinal: Mesenteric artery thrombosis, ischemic colitis.

The oculomucocutaneous syndrome associated with the beta-blocker practolol has not been reported with labetalol HCl.

Clinical Laboratory Tests: There have been reversible increases of serum transaminases in 4% of patients treated with labetalol HCl and tested and, more rarely, reversible increases in blood urea.

OVERDOSAGE

Overdosage with labetalol HCl causes excessive hypotension that is posture sensitive and, sometimes, excessive bradycardia. Patients should be placed supine and their legs raised if necessary to improve the blood supply to the brain. If overdosage with labetalol HCl follows oral ingestion, gastric lavage or pharmacologically induced emesis (using syrup of ipecac) may be useful for removal of the drug shortly after ingestion. The following additional measures should be employed if necessary: Excessive bradycardia—administer atropine or epinephrine. Cardiac failure—administer a digitalis glycoside and a diuretic. Dopamine or dobutamine may also be useful. Hypotension—administer vasopressors, e.g., norepinephrine. There is pharmacologic evidence that norepinephrine may be the drug of choice. Bronchospasm—administer epinephrine and/or an aerosolized beta2-agonist. Seizures—administer diazepam.

In severe beta-blocker overdose resulting in hypotension and/or bradycardia, glucagon has been shown to be effective when administered in large doses (5 mg to 10 mg rapidly over 30 seconds, followed by continuous infusion of 5 mg per hour that can be reduced as the patient improves).

Neither hemodialysis nor peritoneal dialysis removes a significant amount of labetalol HCl from the general circulation (<1%).

The oral LD50 value of labetalol HCl in the mouse is approximately 600 mg/kg and in the rat is >2 g/kg. The IV LD50 in these species is 50 mg/kg to 60 mg/kg.

DOSAGE AND ADMINISTRATION

DOSAGE MUST BE INDIVIDUALIZED. The recommended initial dosage is 100 mg twice daily whether used alone or added to a diuretic regimen. After 2 or 3 days, using standing blood pressure as an indicator, dosage may be titrated in increments of 100 mg twice daily every 2 or 3 days. The usual maintenance dosage of labetalol HCl is between 200 mg and 400 mg twice daily.

Since the full antihypertensive effect of labetalol HCl is usually seen within the first 1 to 3 hours of the initial dose or dose increment, the assurance of a lack of an exaggerated hypotensive response can be clinically established in the office setting. The antihypertensive effects of continued dosing can be measured at subsequent visits, approximately 12 hours after a dose, to determine whether further titration is necessary.

Patients with severe hypertension may require from 1,200 mg to 2,400 mg per day, with or without thiazide diuretics. Should side effects (principally nausea or dizziness) occur with these doses administered twice daily, the same total daily dose administered three times daily may improve tolerability and facilitate further titration. Titration increments should not exceed 200 mg twice daily.

When a diuretic is added, an additive antihypertensive effect can be expected. In some cases this may necessitate a labetalol HCl dosage adjustment. As with most antihypertensive drugs, optimal dosages of Labetalol Hydrochloride Tablets are usually lower in patients also receiving a diuretic.

When transferring patients from other antihypertensive drugs, Labetalol Hydrochloride Tablets should be introduced as recommended and the dosage of the existing therapy progressively decreased.

Elderly Patients

As in the general patient population, labetalol therapy may be initiated at 100 mg twice daily and titrated upwards in increments of 100 mg twice daily as required for control of blood pressure. Since some elderly patients eliminate labetalol more slowly, however, adequate control of blood pressure may be achieved at a lower maintenance dosage compared to the general population. The majority of elderly patients will require between 100 mg and 200 mg twice daily.

HOW SUPPLIED

Product: 50090-4149

NDC: 50090-4149-0 60 TABLET, FILM COATED in a BOTTLE

NDC: 50090-4149-1 90 TABLET, FILM COATED in a BOTTLE

Product of Italy

Distributed by:
Alvogen, Inc.
Pine Brook, NJ 07058 USA

For Inquiries Call: 1-866-770-3024

All trademarks are the property of their respective owners.

PI552-00
Rev. 10/2016

Storage

Labetalol Hydrochloride Tablets should be stored between 2° and 30°C (36° and 86°F).